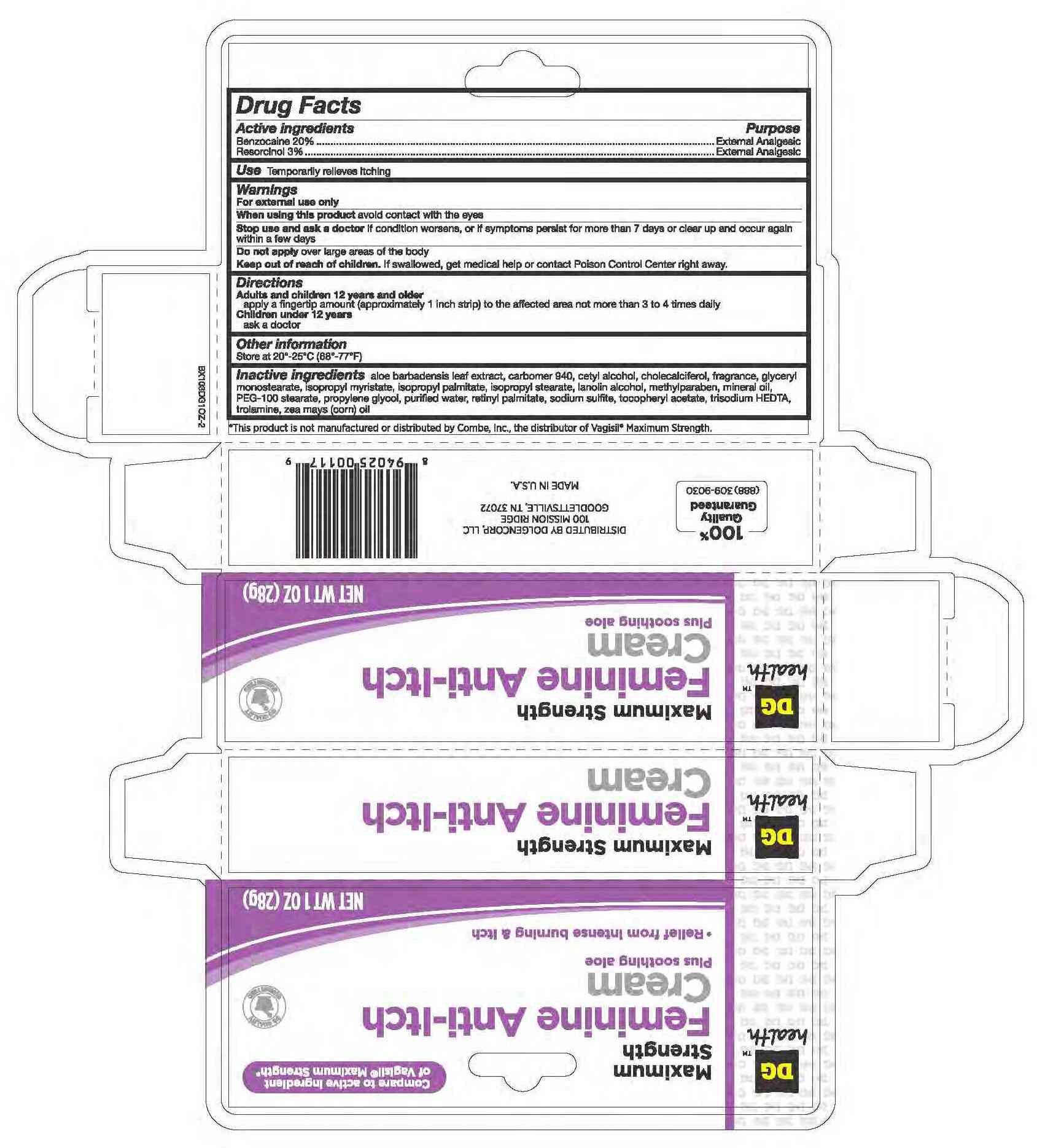 DRUG LABEL: BENZOCAINE and RESORCINOL
NDC: 55910-185 | Form: CREAM
Manufacturer: Dolgencorp, inc
Category: otc | Type: HUMAN OTC DRUG LABEL
Date: 20110701

ACTIVE INGREDIENTS: BENZOCAINE 200 mg/1 g; RESORCINOL 20 mg/1 g
INACTIVE INGREDIENTS: WATER; CARBOMER HOMOPOLYMER TYPE C; CETYL ALCOHOL; GLYCERYL MONOSTEARATE; ISOPROPYL PALMITATE; ISOPROPYL MYRISTATE; ISOPROPYL STEARATE; LANOLIN ALCOHOLS; MINERAL OIL; POLYOXYL 100 STEARATE; VITAMIN A; VITAMIN D; ALOE VERA LEAF; SODIUM SULFITE; ALPHA-TOCOPHEROL; TRISODIUM HEDTA; METHYLPARABEN; PROPYLENE GLYCOL; CORN OIL

drug facts

Active ingredients Purpose
Benzocaine 20%....................External Analgesic
Resorcinol 3%........................External Analgesic

PURPOSE

Use temporarily relieves itching

Keep out of reach of children. If swallowed, get medical help or contact a Poison Control Center right away.

INDICATIONS AND USAGE

Use temporarily relieves itching
Other information - store at 20 degrees - 25 degrees C (68 degrees - 77 degrees F)

Warnings
For external use only.
_______________________________________________________________________________________________________________________
When using this product avoid contact with the eyes
_______________________________________________________________________________________________________________________
Stop use and ask a doctor if condition worsens, or if symptoms persist for more than 7 days or clear up and occur again within a few days
_______________________________________________________________________________________________________________________
Do not apply over large areas of the body
Keep out of reach of children. If swallowed, get medical help or contact a Poison Control Center right away.
_______________________________________________________________________________________________________________________

Directions
adults and children 12 years and older
apply a fingertip amount (approximately 1 inch strip) to the affected area not more than 3 to 4 times daily
children under 12 years
ask a doctor

INACTIVE INGREDIENT

Inactive Ingredients aloe barbadensis leaf extract, carbomer 940, cetyl alcohol, cholecalciferol, fragrance, glyceryl monostearate,
isopropyl myristate, isopropyl palmitate, isopropyl stearate, lanolin alcohol, methylparaben, mineral oil, PEG-100 stearate, propylene glycol,
purified water, retinyl palmitate, sodium sulfite, tocopheryl acetate, trisodium HEDTA, trolamine, zea mays (corn) oil